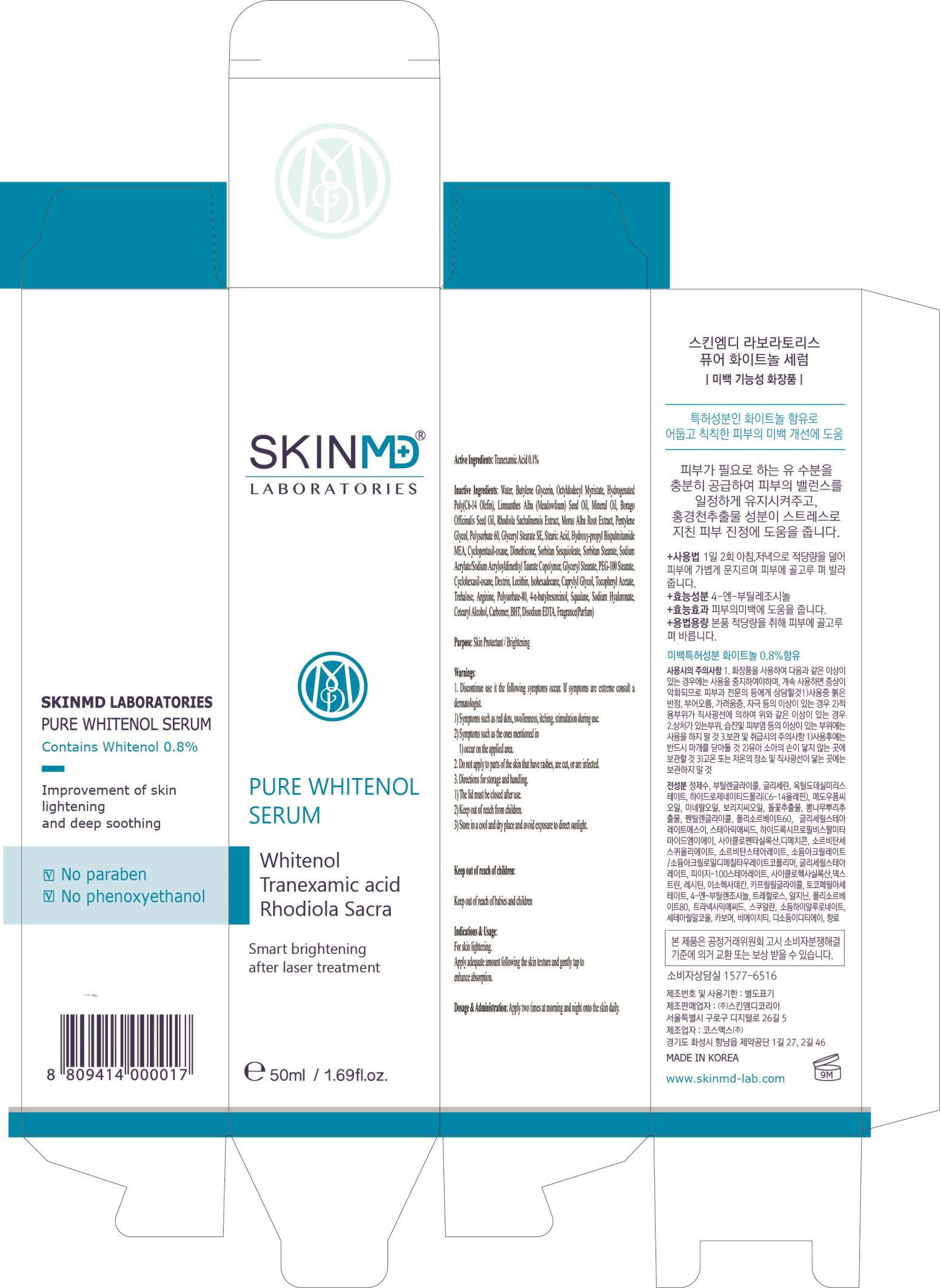 DRUG LABEL: Pure Whitenol Serum
NDC: 69629-010 | Form: CREAM
Manufacturer: SKIN M.D. KOREA
Category: otc | Type: HUMAN OTC DRUG LABEL
Date: 20150306

ACTIVE INGREDIENTS: Tranexamic Acid 0.05 mg/50 mL
INACTIVE INGREDIENTS: Water; Mineral Oil

ACTIVE INGREDIENT

Active Ingredients: Tranexamic Acid 0.1%

INACTIVE INGREDIENT

Inactive Ingredients: Water, Butylene Glycerin, Octyldodecyl Myristate, Hydrogenated Poly(C6-14 Olefin), Limnanthes Alba (Meadowfoam) Seed Oil, Mineral Oil, Borago Officinalis Seed Oil, Rhodiola Sachalinensis Extract, Morus Alba Root Extract, Pentylene Glycol, Polysorbate 60, Glyceryl Stearate SE, Stearic Acid, Hydroxy-propyl Bispalmitamide MEA, Cyclopentasil-oxane, Dimethicone, Sorbitan Sesquioleate, Sorbitan Stearate, Sodium Acrylate/Sodium Acryloyldimethyl Taurate Copolymer, Glyceryl Stearate, PEG-100 Stearate, Cyclohexasil-oxane, Dextrin, Lecithin, Isohexadecane, Caprylyl Glycol, Tocopheryl Acetate, Trehalose, Arginine, Polysorbate-80, 4-n-butylresorcinol, Squalane, Sodium Hyaluronate, Cetearyl Alcohol, Carbomer, BHT, Disodium EDTA, Fragrance(Parfum)

PURPOSE

Purpose: Skin Protectant / Brightening

WARNINGS

1. Discontinue use it the following symptoms occur. If symptoms are extreme consult a dermatologist.

1) Symptoms such as red dots, swollenness, itching, stimulation during use.

2) Symptoms such as the ones mentioned in 1) occur on the applied area.

2. Do not apply to parts of the skin that have rashes, are cut, or are infected.

3. Directions for storage and handling.

1) The lid must be closed after use.

2) Keep out of reach from children.

3) Store in a cool and dry place and avoid exposure to direct sunlight.

Keep out of reach of children: Keep out of reach of babies and children

INDICATIONS & USAGE

Indications & Usage: For skin lightening. Apply adequate amount following the skin texture and gently tap to enhance absorption.

DOSAGE & ADMINISTRATION

Dosage & Administration: Apply two times at morning and night onto the skin daily.

PACKAGE LABEL.PRINCIPAL DISPLAY PANEL

Image of carton